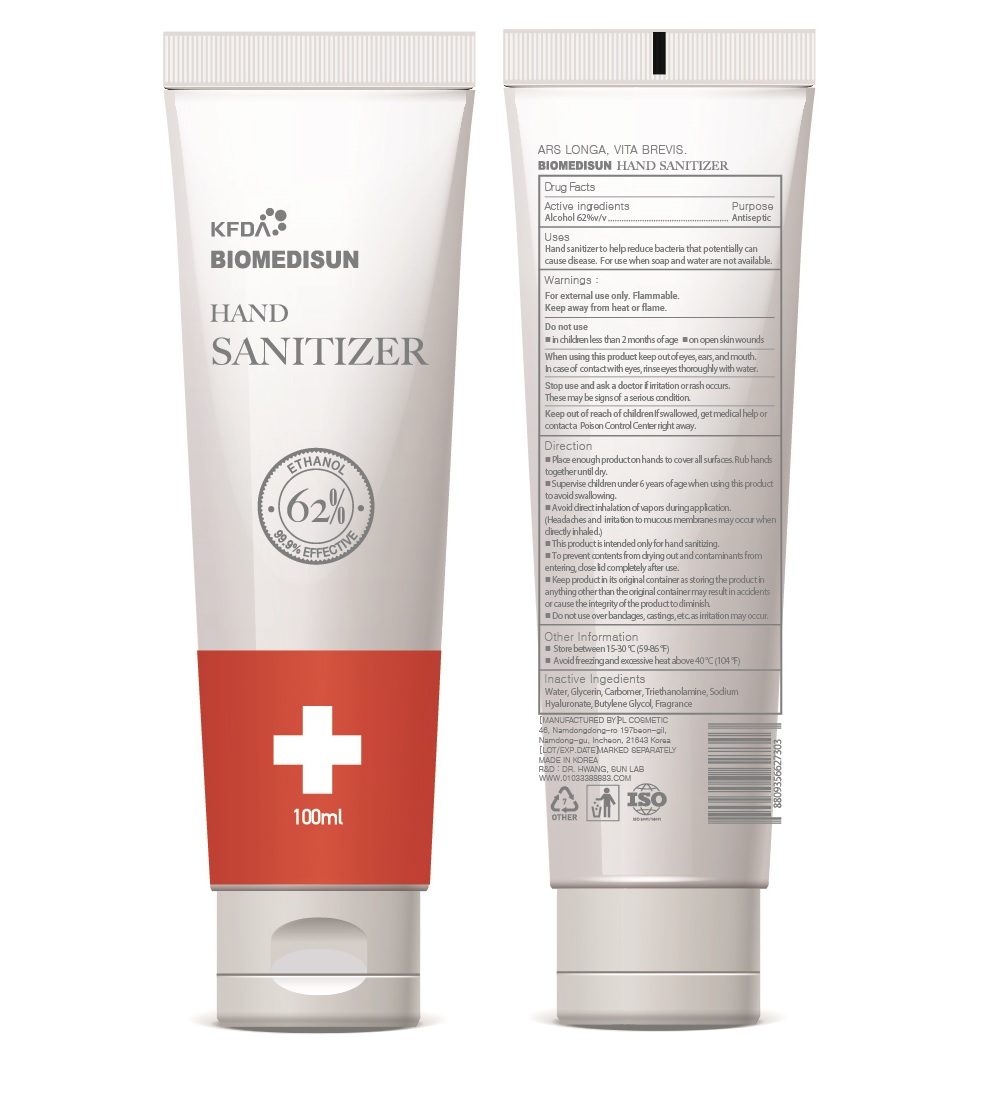 DRUG LABEL: BIOMEDISUN HAND SANITIZER
NDC: 74339-4162 | Form: GEL
Manufacturer: PL COSMETIC
Category: otc | Type: HUMAN OTC DRUG LABEL
Date: 20200406

ACTIVE INGREDIENTS: ALCOHOL 62 mL/100 mL
INACTIVE INGREDIENTS: GLYCERIN; CARBOMER HOMOPOLYMER, UNSPECIFIED TYPE; WATER; BUTYLENE GLYCOL; HYALURONATE SODIUM; TROLAMINE

[BIOMEDISUN] 100 ml TUBE TYPE 62: 74339-4162